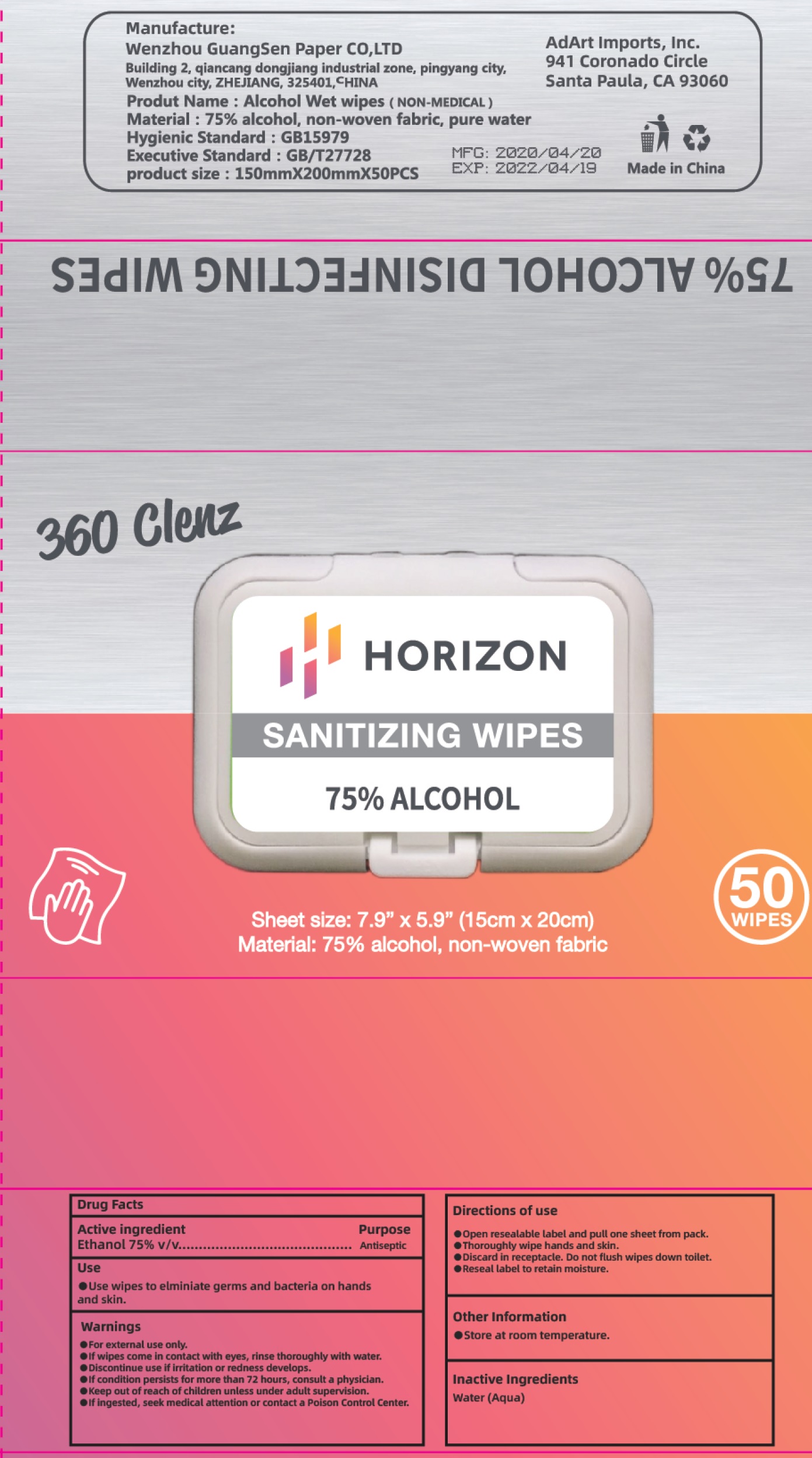 DRUG LABEL: Horizon Sanitizing Wipes
NDC: 77469-003 | Form: CLOTH
Manufacturer: AdArt Imports, Inc.
Category: otc | Type: HUMAN OTC DRUG LABEL
Date: 20200706

ACTIVE INGREDIENTS: ALCOHOL 0.75 mL/1 mL
INACTIVE INGREDIENTS: WATER

Horizon Sanitizing Wipes

Active ingredient

Ethanol 75% v/v

Purpose

Antiseptic

Use

- Use wipes to elminiate germs and baceria on hands and skin.

Warnings

- For external use only.
- If wipes come in contact with eyes, rinse thoroughly with water.
- Disocontinue use if irritation or redness develops.
- If condition persists for more than 72 hours, consult a physician,.

Keep out of reach of children

- unless under adult supervision.
- If ingested, seek medical attention or contact a Poison Control Center.

Directions Of Use

- open resealable label and pull one sheet from pack.
- Thoroughly wipe hands and skin.
- Discard in receptacle. Do not flush wipes down toilet.
- Reseal label to retain moisture.

Other Information

- Store at room temperature.

Inactive Ingredients

Water (Aqua)